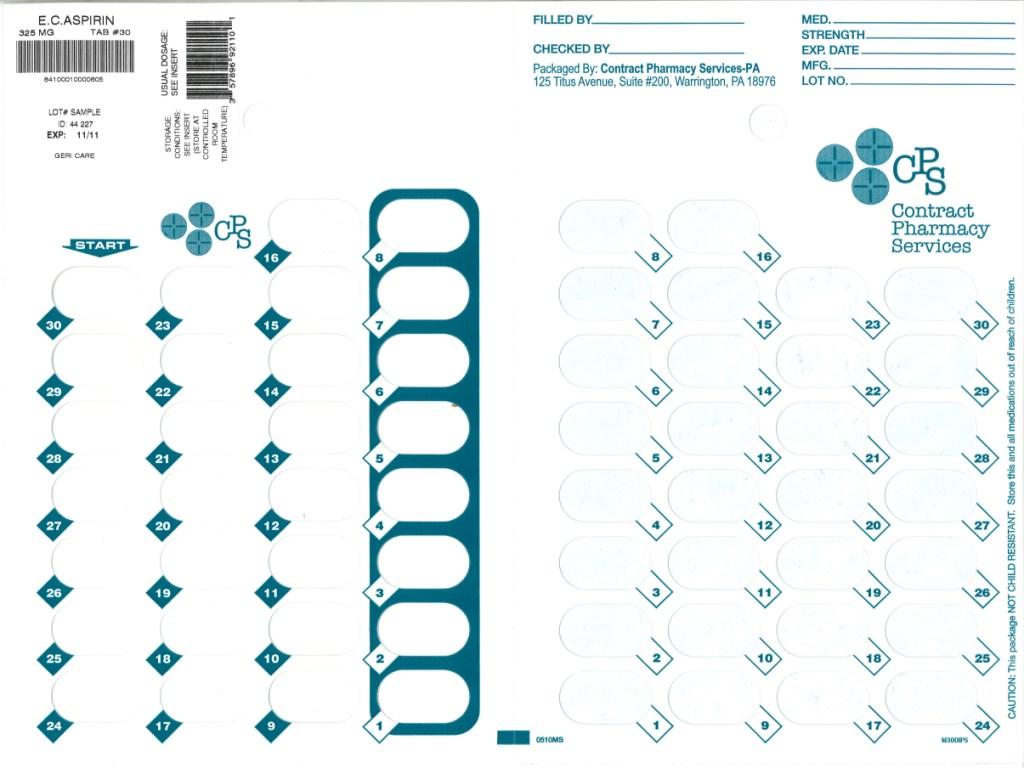 DRUG LABEL: ASPIRIN
NDC: 67046-164 | Form: TABLET, FILM COATED
Manufacturer: Contract Pharmacy Services-PA
Category: otc | Type: HUMAN OTC DRUG LABEL
Date: 20101102

ACTIVE INGREDIENTS: ASPIRIN 325 mg/1 1
INACTIVE INGREDIENTS: POWDERED CELLULOSE; CROSCARMELLOSE SODIUM; D&C YELLOW NO. 10; FD&C YELLOW NO. 6; HYPROMELLOSES; FERRIC OXIDE RED; METHACRYLIC ACID; MINERAL OIL; POLYDEXTROSE; POLYSORBATE 80; PROPYLENE GLYCOL; SILICON DIOXIDE; SODIUM ALGINATE; SODIUM BICARBONATE; SODIUM LAURYL SULFATE; STEARIC ACID; TALC; TITANIUM DIOXIDE; TRIACETIN; TRIETHYL CITRATE

Aspirin Tablets

ACTIVE INGREDIENT (IN EACH TABLET)

Aspirin 325 mg (NSAID*)

*nonsteroidal anti-inflammatory drug

PURPOSE

Pain reliever/fever reducer

USES

Temporarily relieves minor aches and pains associated with

- headache
- minor arthritis
- common cold
- menstrual cramps
- muscular aches
- backache
- toothache

Temporarily reduces fever.

WARNINGS

Reye’s syndrome: Children and teenagers who have or are recovering from chicken pox or flu-like symptoms should not use this product. When using this product, if changes in behavior with nausea and vomiting occur, consult a doctor because these symptoms could be an early sign of Reye’s syndrome, a rare but serious illness.

Allergy alert: Aspirin may cause a severe allergic reaction which may include:

- hives
- facial swelling
- asthma (wheezing)
- shock

Stomach bleeding warning: This product contains a nonsteroidal anti-inflammatory drug (NSAID), which may cause severe stomach bleeding. The chance is higher if you

- are age 60 or older
- have had stomach ulcers or bleeding problems
- take a blood thinning (anticoagulant) or steroid drug
- take other drugs containing prescription or nonprescription NSAIDs (aspirin, ibuprofen, naproxen, or others)
- have 3 or more alcoholic drinks every day while using this product
- take more or for a longer time than directed

Do not use

• if you are allergic to aspirin or any other pain reliever/fever reducer

Ask a doctor before use if

- stomach bleeding warning applies to you
- you have a history of stomach problems, such as heartburn
- you have high blood pressure, heart disease, liver cirrhosis, or kidney disease
- you are taking a diuretic

Ask a doctor or pharmacist before use if

taking a prescription drug for diabetes, gout or arthritis

Stop use and ask a doctor if

- you experience any of the following signs of stomach bleeding:
- feel faint
- vomit blood
- have bloody or black stools
- have stomach pain that does not get better
- pain gets worse or lasts for more than 10 days
- redness or swelling is present
- any new symptoms appear
- ringing in the ears or loss of hearing occurs

If pregnant or breast-feeding,

ask a health professional before use. It is especially important not to use aspirin during the last 3 months of pregnancy unless definitely directed to do so by a doctor because it may cause problems in the unborn child or complications during delivery.

Keep out of reach of children.

Overdose warning: Taking more than the recommended dose (overdose) may cause liver damage. In case of overdose, get medical help or contact a Poison Control Center right away. (1-800-222-1222). Quick medical attention is critical for adults as well as for children even if you do not notice any signs or symptoms.

DIRECTIONS

- do not take more than directed
- the smallest effective dose should be used
- do not take longer than 10 days, unless
  directed by a doctor (see Warnings)
- drink a full glass of water with each dose

Adults and childre: (12 years and older)

Take 1 or 2 tablets with water every 4 hours as needed. Do not take more than 12 tablets in 24 hours, or as directed by a doctor.

Children under 12 years:

Do not give to children under 12 years of age.

OTHER INFORMATION

store at 15° to 30°C (59° to 86°F)

Inactive Ingredients

ma contain acetylated monoglycerides, cellulose, croscarmellose sodium, D&C yellow #10 lake, FD&C yellow lake #6, hypromellose, hypromellose phthalate, iron oxide, methacrylic acid, mineral oil, PEG, polydextrose, polysorbate 80, polyvinyl acetate phthalate, propylene glycol, silica, sodium alginate, sodium bicarbonate, sodium lauryl sulfate, starch, stearic acid, talc, titanium dioxide, triacetin, triethyl citrate, wax.

QUESTIONS OR COMMENTS?

Distributed by:

GERI-CARE PHARMACEUTICALS CORP.

1650 63 Street, Brooklyn, New York 11204

Repackaged by:
Contract Pharmacy Services-PA
125 Titus Ave Suite 200
Warrington, PA 18976 USA

Original--08/2010--NJW

Package Label

Blister of 30 Tablets